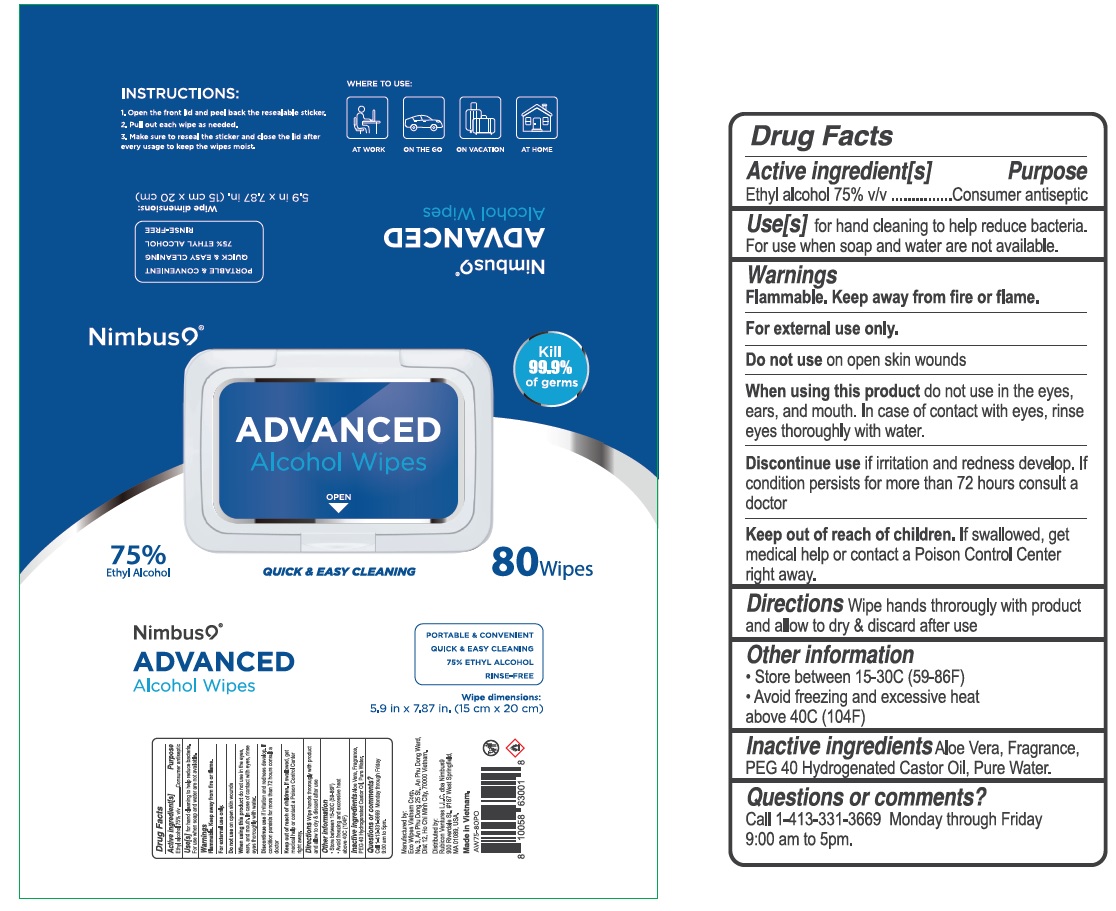 DRUG LABEL: Nimbus9 Advanced Alcohol Wipes Pouch 80pcs
NDC: 78898-675 | Form: CLOTH
Manufacturer: Eco Wipes Vietnam Corporation
Category: otc | Type: HUMAN OTC DRUG LABEL
Date: 20200901

ACTIVE INGREDIENTS: ALCOHOL 75 mL/100 mL
INACTIVE INGREDIENTS: ALOE VERA LEAF; POLYOXYL 40 HYDROGENATED CASTOR OIL; WATER

Nimbus9® ADVANCED Alcohol Wipes

Active ingredient[s]

Ethyl alcohol 75% v/v

Purpose

Consumer antiseptic

INDICATIONS AND USAGE

Use[s] for hand cleaning to help reduce bacteria. For use when soap and water are not available.

Warnings

Flammable. Keep away from fire or flame.

For external use only.

Do not use on open skin wounds

When using this product do not use in the eyes, ears, and mouth. In case of contact with eyes, rinse eyes thoroughly with water.

Discontinue use if irritation and redness develop. If condition persists for more than 72 hours consult a doctor

Keep out of reach of children. If swallowed, get medical help or contact a Poison Control Center right away.

DOSAGE AND ADMINISTRATION

Directions Wipe hands thoroughly with product and allow to dry & discard after use

Other information

• Store between 15-30C (59-86F)

• Avoid freezing and excessive heat above 40C (104F)

INACTIVE INGREDIENT

Inactive ingredients Aloe Vera, Fragrance, PEG 40 Hydrogenated Castor Oil, Pure Water.

Questions or comments?

Call 1-413-331-3669 Monday through Friday 9:00 am to 5pm.

QUICK & EASY CLEANING

75% ETHYL ALCOHOL

Kill 99.9% of germs

PORTABLE & CONVENIENT

RINSE-FREE

INSTRUCTIONS:

1. Open the front lid and peel back the resealable sticker.

2. Pull out each wipe as needed.

3. Make sure to reseal the sticker and close the lid after every usage to keep the wipes moist.

WHERE TO USE:

AT WORK

ON THE GO

ON VACATION

AT HOME

Manufactured by:

Eco Wipes Vietnam Corp.

No. 3, An Phu Dong 25 St., An Phu Dong Ward,

Dist 12, Ho Chi Minh City, 70000 Vietnam.

Distributed by:

Rubicon Ventures L.L.C. dba Nimbus9

900 Riverdale St., #187 West Springfield,

MA 01089, USA.

Made in Vietnam.